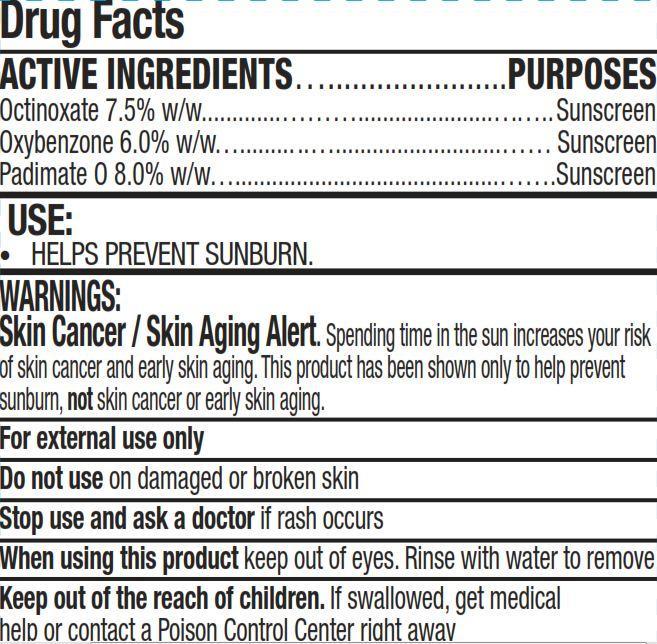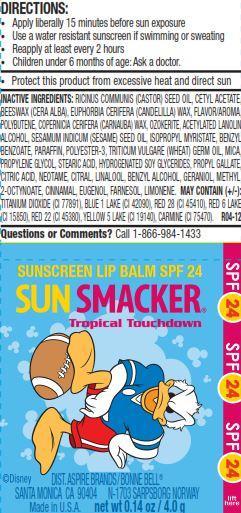 DRUG LABEL: Donald Duck Sun Smacker SPF 24 Tropical Touchdown
                
NDC: 50051-0004 | Form: LIPSTICK
Manufacturer: Bonne Bell LLC
Category: otc | Type: HUMAN OTC DRUG LABEL
Date: 20120906

ACTIVE INGREDIENTS: OCTINOXATE 7.5 g/100 g; OXYBENZONE 6 g/100 g; PADIMATE O 8 g/100 g
INACTIVE INGREDIENTS: CASTOR OIL; CETYL ACETATE; YELLOW WAX; CANDELILLA WAX; CARNAUBA WAX; ACETYLATED LANOLIN ALCOHOLS; SESAME OIL; ISOPROPYL MYRISTATE; BENZYL BENZOATE; PARAFFIN; WHEAT GERM OIL; MICA; PROPYLENE GLYCOL; STEARIC ACID; PROPYL GALLATE; CITRIC ACID MONOHYDRATE; NEOTAME; CITRAL; LINALOOL, (+/-)-; BENZYL ALCOHOL; GERANIOL; METHYL HEPTINE CARBONATE; CINNAMALDEHYDE; EUGENOL; FARNESOL; TITANIUM DIOXIDE; D&C RED NO. 28; D&C RED NO. 22; D&C RED NO. 6; FD&C YELLOW NO. 5

Donald Duck Sun Smacker SPF 24 Tropical Touchdown

Drug Facts

ACTIVE INGREDIENTS

Octinoxate 7.5 percent w per w

Oxybenzone 6.0 percent w per w

Padimate 0 8.0 percent w per w

PURPOSES

Sunscreen

USE

HELPS PREVENT SUNBURN.

WARNINGS

Skin Cancer Skin Aging Alert. Spending time in the sun increases your risk of skin cancer and early skin aging. This product has been shown only to help prevent sunburn, not skin cancer or early skin aging.

For external use only

Do not use

on damaged or broken skin

Stop use and ask a doctor

if rash occurs

When using this product

keep out of eyes. Rinse with water to remove

Keep out of the reach of children.

If swallowed, get medical help or contact a Poison Control Center right away

DIRECTIONS

- Apply liberally 15 minutes before sun exposure
- Use a water resistant sunscreen if swimming or sweating
- Reapply at least every 2 hours
- Children under 6 months of age: Ask a doctor.

Storage and Handling

Protect this product from excessive heat and direct sun

INACTIVE INGREDIENTS

RICINUS COMMUNIS (CASTOR) SEED OIL, CETYL ACETATE, BEESWAX (CERA ALBA), EUPHORBIA CERIFERA (CANDELILLA) WAX, FLAVOR/AROMA, POLYBUTENE, COPERNICIA CERIFERA (CARNAUBA) WAX, OZOKERITE, ACETYLATED LANOLIN ALCOHOL, SESAMUM INDICUM (SESAME) SEED OIL, ISOPROPYL MYRISTATE, BENZYL BENZOATE, PARAFFIN, POLYESTER-3, TRITICUM VULGARE (WHEAT) GERM OIL, MICA, PROPYLENE GLYCOL, STEARIC ACID, HYDROGENATED SOY GLYCERIDES, PROPYL GALLATE, CITRIC ACID, NEOTAME, CITRAL, LINALOOL, BENZYL ALCOHOL, GERANIOL, METHYL 2-OCTYNOATE, CINNAMAL, EUGENOL, FARNESOL, LIMONENE. MAY CONTAIN (PLUS OR MINUS) TITANIUM DIOXIDE (CI 77891), BLUE 1 LAKE (CI 42090), RED 28 (CI 45410), RED 6 LAKE (CI 15850), RED 22 (CI 45380), YELLOW 5 LAKE (CI 19140), CARMINE (CI 75470).

Questions or Comments

Call 1-866-984-1433

Package Label

SUNSCREEN LIP BALM SPF 24
SUN SMACKER
Tropical Touchdown
(c) Disney
DIST. ASPIRE BRANDS/BONNE BELL (R)
SANTA MONICA CA 90404 N-1703 SARPSBORG NORWAY
Made in U.S.A. net wt 0.14 oz 4.0 g